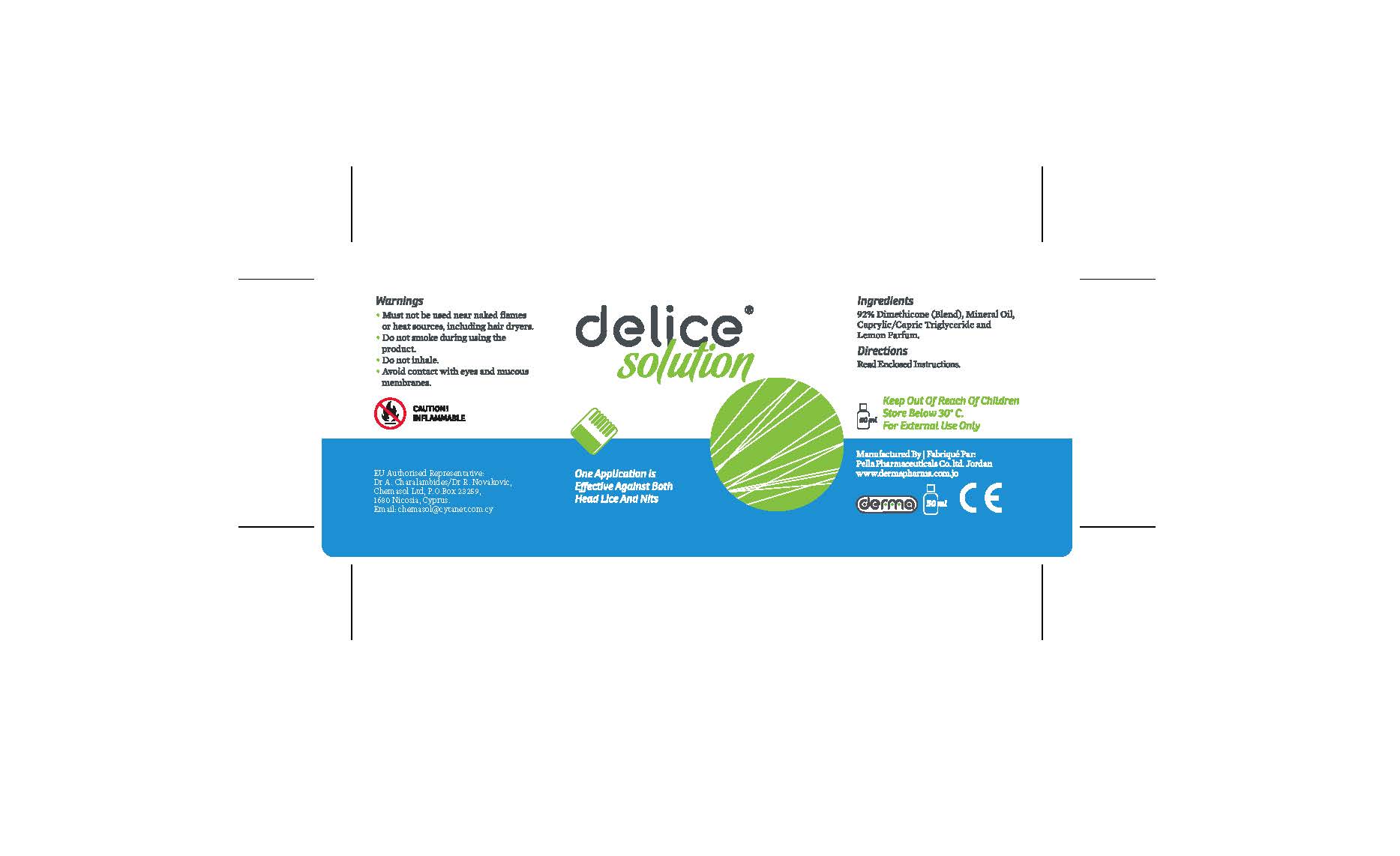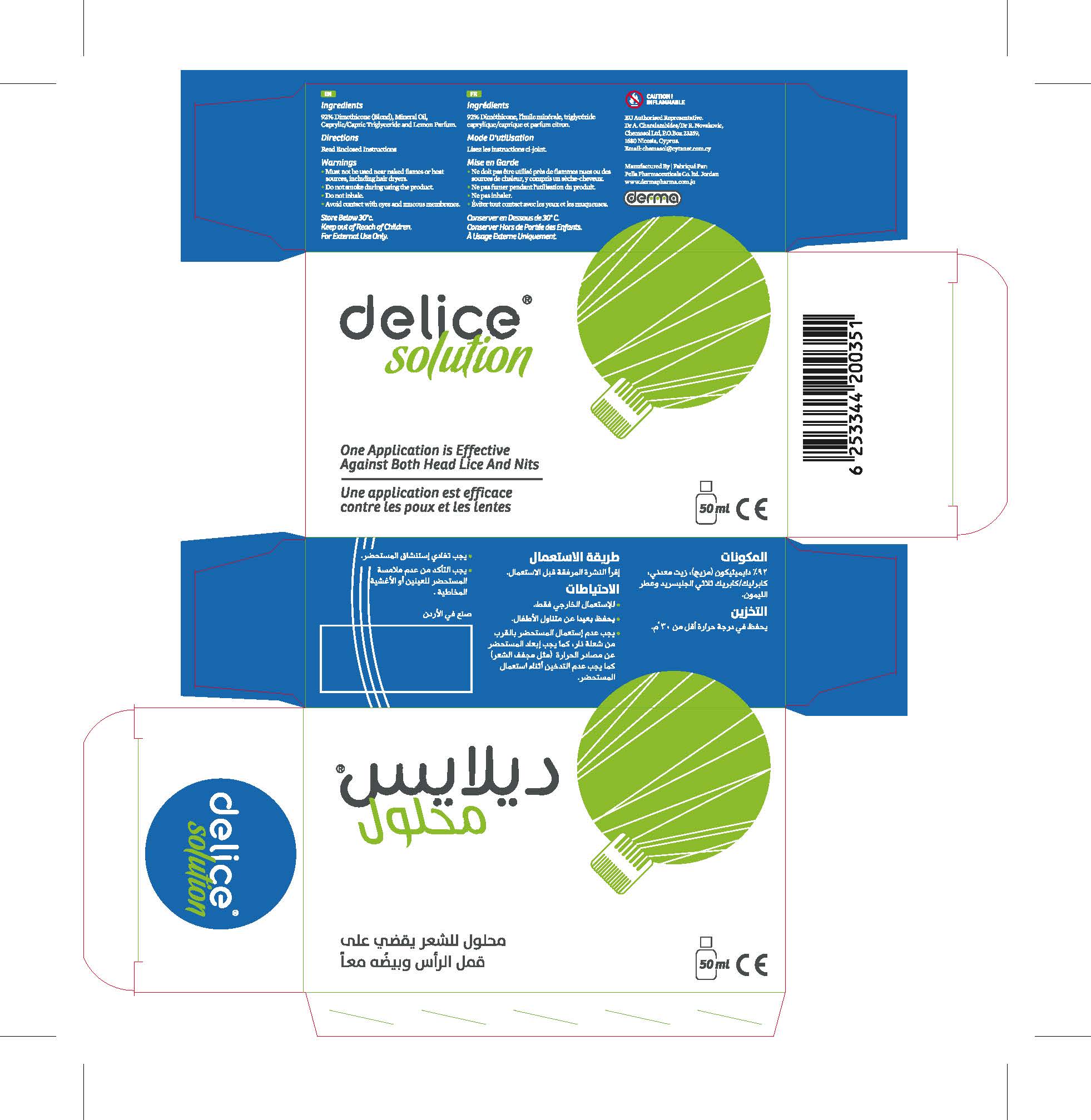 DRUG LABEL: Delice
NDC: 82160-351 | Form: SOLUTION
Manufacturer: Pella Pharmaceuticals Co. Ltd
Category: otc | Type: HUMAN OTC DRUG LABEL
Date: 20241231

ACTIVE INGREDIENTS: DIMETHICONE 100 25 g/50 mL; DIMETHICONE 21 g/50 mL
INACTIVE INGREDIENTS: MINERAL OIL; MEDIUM-CHAIN TRIGLYCERIDES; FRAGRANCE LEMON ORC2001060

Delice

Active Ingredient

Dimethicone (Blend) 92%

Composition

Mineral Oil, Caprylic/ Capric Triglyceride and Lemon Fragrance.

Characteristics

Delice® does not contain any harmful insecticides.The solutioncreeps deeply into the breathing syatem of lice, nymphs and eggs (nits) resultingin suffocation. Because this mechanism of action is physical, the development of resistance inlice is not possible.

Indications

Delice® is a physical treatment of scalp hair in case of infestation with head lice; if used as instructedit is also effective against nymphs and eggs (nits).

Contraindications

Delice® must not be used in people with known hypersensitivity to any of its ingredients.

If any allergic skin reactions should occur, treatment should be stopped immediately.

Delice® should not be used in children under the age of two years because thee s no enoughstudies demonstrate the safety use on this group.

Precautions

Delice® is for external use only.

Avoid inhaling Delice®.

Precaution

Keep out of reach of children

Warnings

When using Delice®, you should make sure that the solution does not come into contact with eyes or mucous membranes (nose and throat). if the solution gets into the eyes accidently, rinse for 10 - 15 minutes with plenty of water. If irritation persists please consult your doctor or pharmacist.

Because some ingredients are flammable, Delice® must not be used near naked flames or heat sources, including hair dryers. Keep Delice® away from sources of ignition and do not smoke during using this product.

If Delice® spilled accidently, there is danger of slipping. Spillage should therefore be cleaned up immediately.

Pregnancy

Delice® should not be used in pregnant women because there is no enough studies demonstrate the safety use on these groups.

Lactation

Delice® should not be used in breast-feeding women because there is no enough studies demonstrate the safety use on these groups.

Interactions

Delice® could react with certain hair care and hair tinting products.

Side Effects

In rare cases, allergic skin reactions can be triggered by one of the ingredientsof Delice®. These occur as inflammation, sewlling, redeness or rashes.

Storage Conditions

Store below 30°C.

Presentation

Glass bottle 50 ml, despensing pump and special comb.

Instructions

Before Delice® is used for the first time; the enclosed dispensing pump must be screwed onto the glass bottle. To do this, remove the screw cap from the bottle and screw the dispensing pumpon tight. Always hold the spray bottle upright or the pump will not be able to work properly. Please note that the pump will need to primed, by pumping, when used for the first time and when used it has been unused for a long period. Inspect all scalp hair of each family member with the Delice® comb. All affected family members must use Delice® on the same day to avoid re-infestation. Delice® comb should be cleaned thoroughly after use.

1. Spray Delice® on the hair and leave it for 30 minutes.

Use Delice on a dry hair; spray the product on overall the hair with scalp massaging by using the inserted comb, to work effectively, whole hair should be wetted by Delice completely, so the product reaches all the lice, egges and nits. The amount of used product depends on the hair length and density. Make sure that the hair near the scalp and behind the ears is covered by the product because the lice and nits are concentrated there. Leave Delice on hair for 30 minutes.

2. After 30 minutes, comb the hair carefully using the lice comb.

After leaving Delice on hair for 30 minutes minimum, comb the hair by using the inserted comb to remove the strangled lice, Delice solution makes the hair combing easier, because it contains ingredients which make the combing hair regardless its length easier.

What is the right way to use the lice comb?

Divide the hair into several parts, and each part in several smaller strands of hair, comb each strand separately with the hair roots and ending with spikes, attach each combed strand backwards, and clean the comb after each strand combing with tissues before resuming combing the other strands.

3. Do not wash out leave the hair to dry at least 8 hours (overnights).

Lice eggs are more flexible and difficult to remove it, Lice makes lice eggs adhere with hair like small balls with white heads, in addition it secretes an adhesive material similar to the composition of hair, even good combing is not enough to remove all the eggs, so you should leave Delice on hair for 8 hours, even the most stubborn eggs will choke.

4. Wash out with normal commercial shampoo.

You can wash Delice solution from hair after eight hours by using any normal shampoo, any traces of solution remains on the hair after the first washing can be easily removed by a second washing.

5. After 8-10 days, re-apply if necessary.

To ensure that all lice and eggs are treated, you must re-apply using the solution by the same procedure which described above. Delice use is safe and you can reuse it many times if necessary.